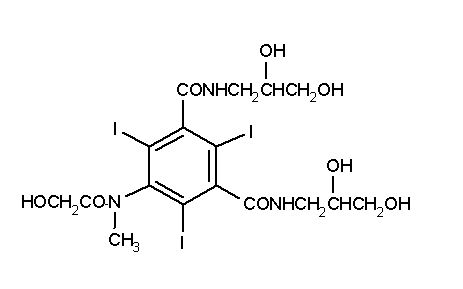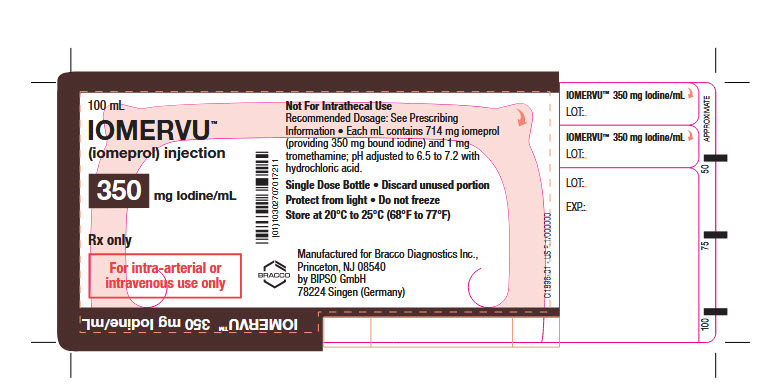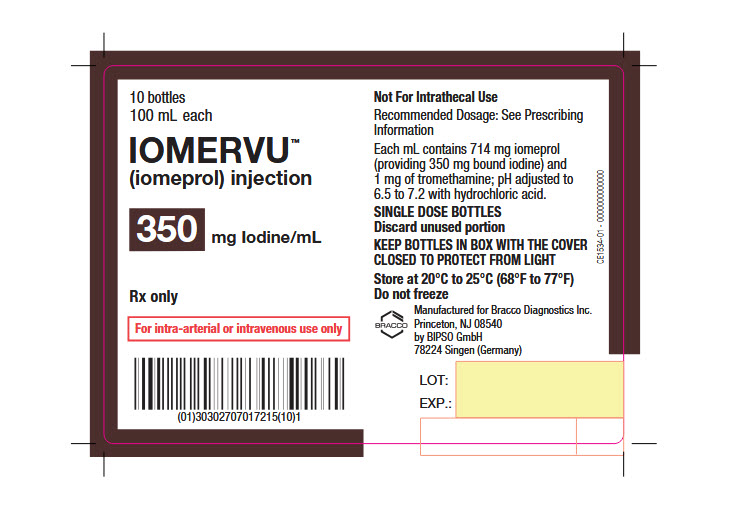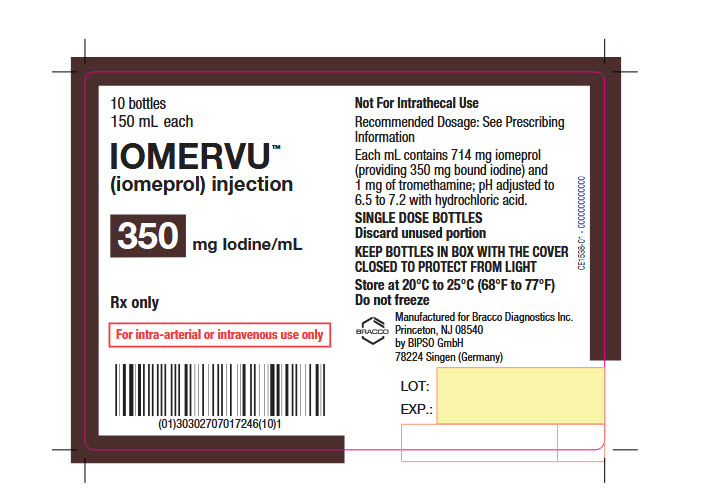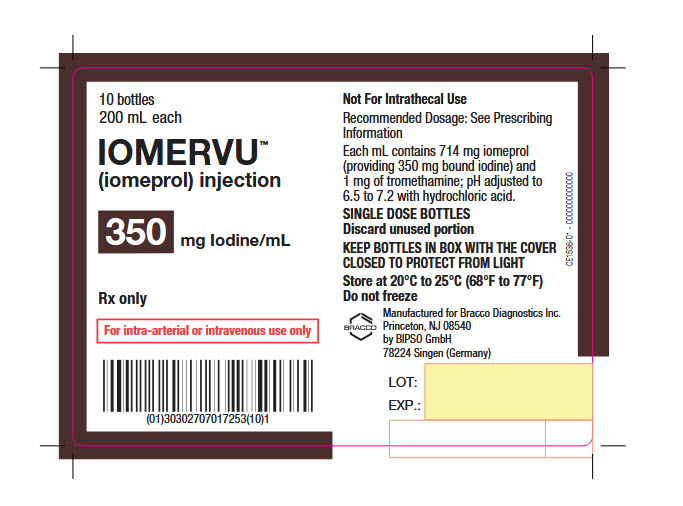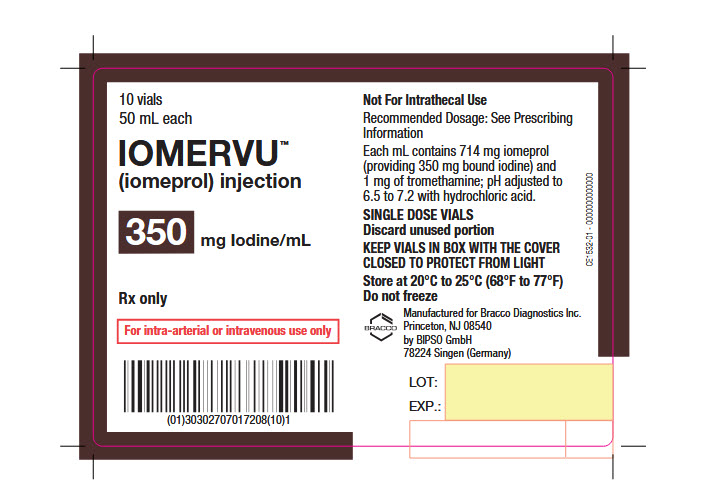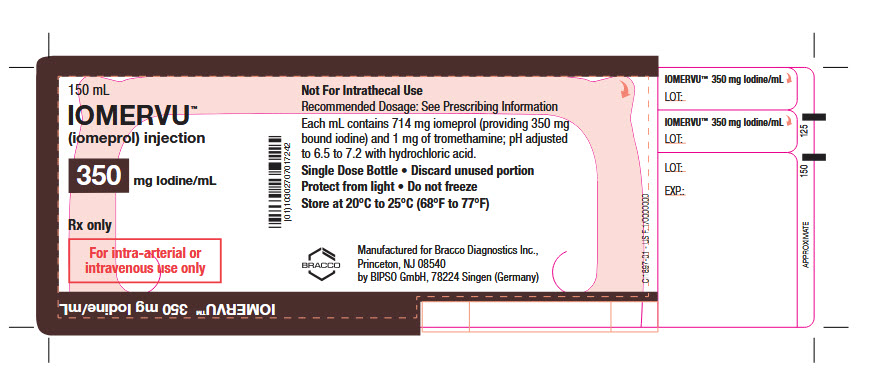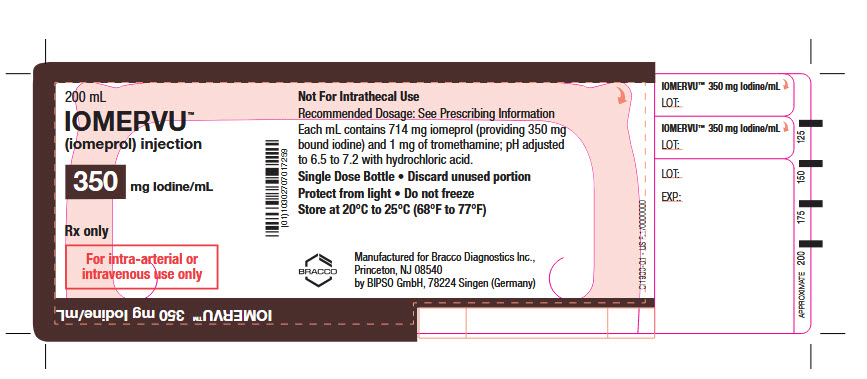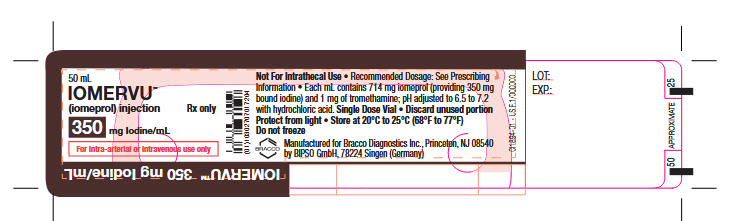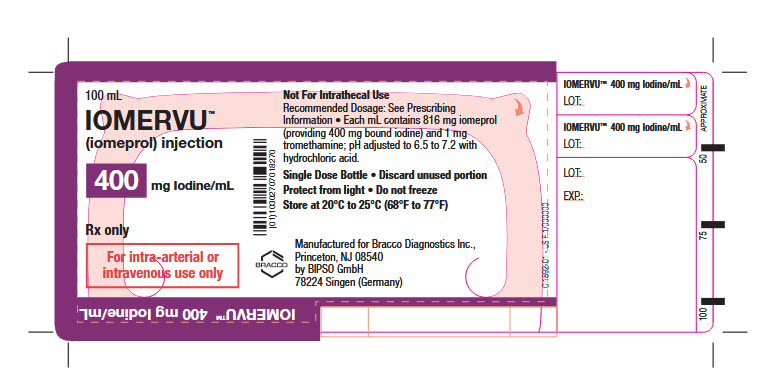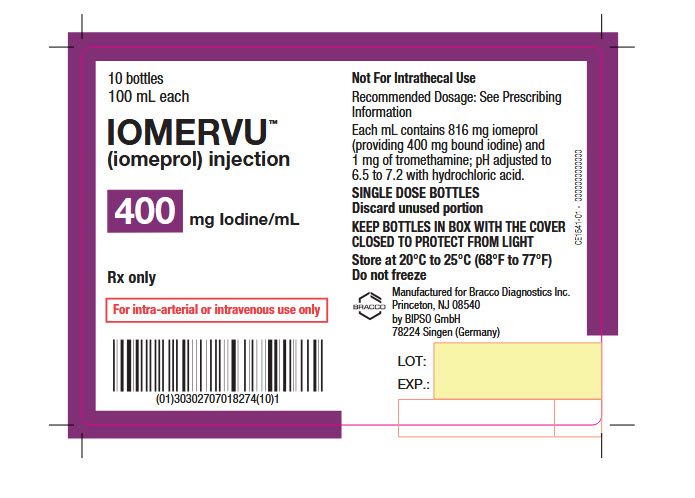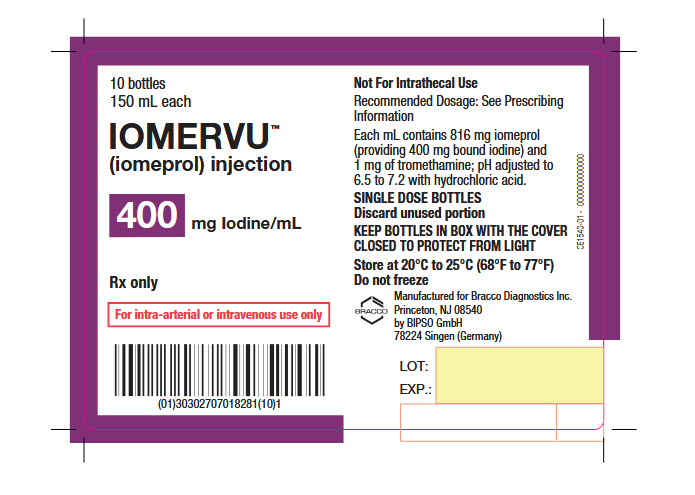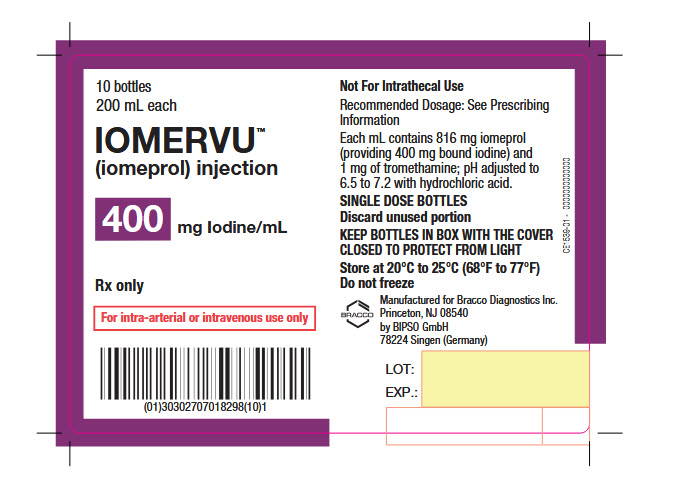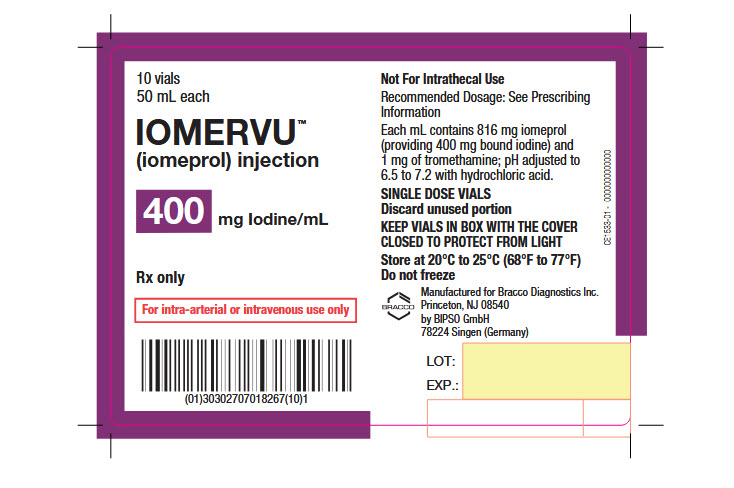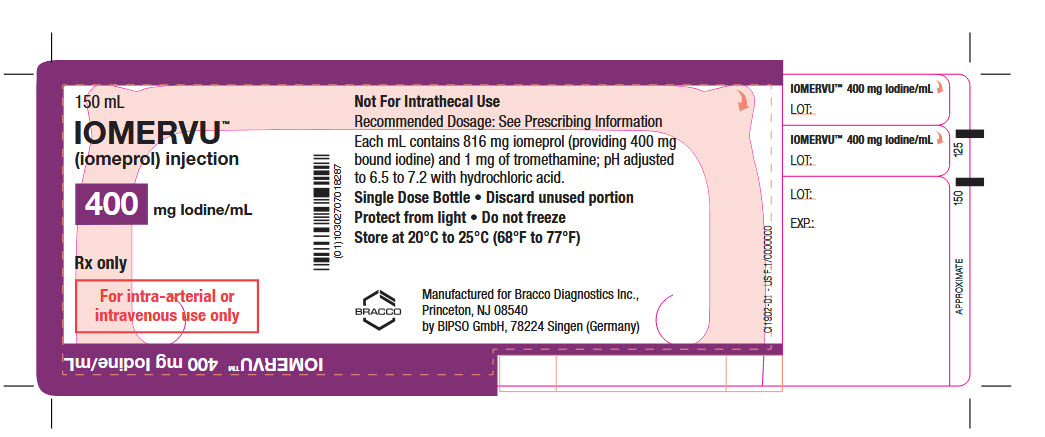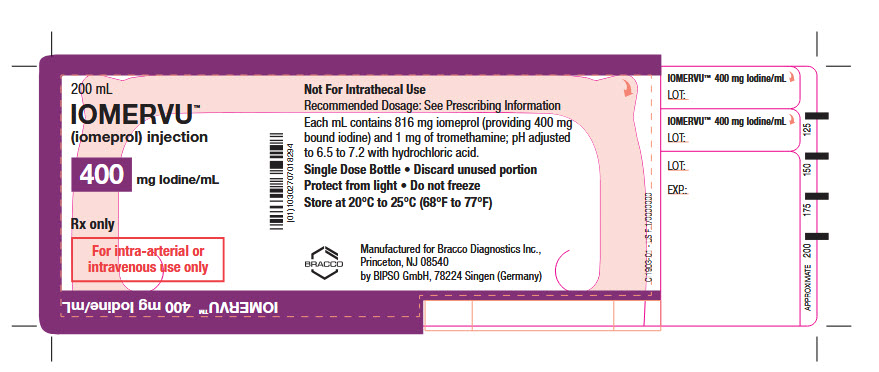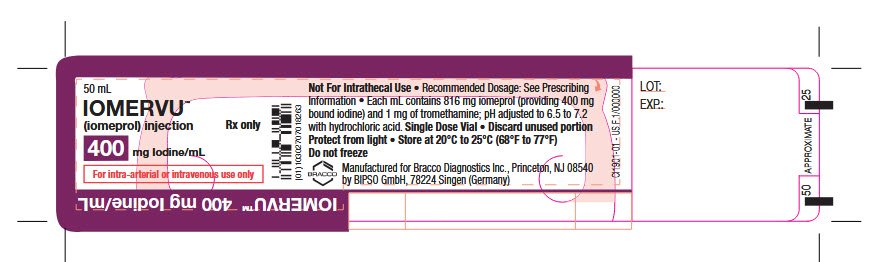 DRUG LABEL: IOMERVU
NDC: 76381-017 | Form: INJECTION, SOLUTION
Manufacturer: BIPSO GmbH
Category: prescription | Type: HUMAN PRESCRIPTION DRUG LABEL
Date: 20260209

ACTIVE INGREDIENTS: IOMEPROL 714 mg/1 mL
INACTIVE INGREDIENTS: TROMETHAMINE 1 mg/1 mL

HIGHLIGHTS OF PRESCRIBING INFORMATION

These highlights do not include all the information needed to use IOMERVU safely and effectively. See full prescribing information for IOMERVU.
IOMERVUTM (iomeprol) injection, for intra-arterial or intravenous use
Initial U.S. Approval: 2024

WARNING: RISKS ASSOCIATED WITH INTRATHECAL ADMINISTRATION

Intrathecal administration, even if inadvertent, may cause death, convulsions, cerebral hemorrhage, coma, paralysis, arachnoiditis, acute renal failure, cardiac arrest, seizures, rhabdomyolysis, hyperthermia, and brain edema. IOMERVU is for intra-arterial or intravenous use only. (2.1, 5.1)

1 INDICATIONS AND USAGE

IOMERVU is a radiographic contrast agent indicated for:
Intra-arterial Procedures† (1.1)

- Cerebral arteriography, includingintra-arterial digital subtraction angiography (IA-DSA), in adults and pediatric patients
- Visceral and peripheral arteriography and aortography, including IA-DSA, in adults and pediatric patients
- Coronary arteriography and cardiac ventriculography in adults
- Radiographic evaluation of cardiac chambers and related arteries in pediatric patients

Intravenous Procedures† (1.2)

- Computed tomography (CT) of the head and body in adults and pediatric patients
- CT angiography of intracranial, visceral, and lower extremity arteries in adults and pediatric patients
- Coronary CT angiography in adults and pediatric patients
- CT urography in adults and pediatric patients

†Specific concentrations are recommended for each type of imaging procedure. (2.2, 2.3, 2.4, 2.5)

2 DOSAGE AND ADMINISTRATION

- Individualize the volume and concentration according to the specific dosing tables accounting for factors such as age, body weight, vessel size, rate of blood flow within the vessel, and structures or areas to be examined. (2.2, 2.3, 2.4, 2.5)
- See full prescribing information for complete dosage and administration information. (2)

3 DOSAGE FORMS AND STRENGTHS

Injection: 250 mg Iodine/mL, 300 mg Iodine/mL, 350 mg Iodine/mL, and 400 mg Iodine/mL in single-dose vials or bottles (3)

4 CONTRAINDICATIONS

None (4)

5 WARNINGS AND PRECAUTIONS

- Hypersensitivity Reactions: Life-threatening or fatal reactions can occur. Always have emergency resuscitation equipment and trained personnel available. (5.2)
- Acute Kidney Injury: Acute injury including renal failure can occur. Minimize dose and maintain adequate hydration to minimize risk. (5.3)
- Cardiovascular Adverse Reactions: Hemodynamic disturbances including shock and cardiac arrest may occur during or after administration. (5.4)
- Thyroid Dysfunction in Pediatric Patients 0 Years to 3 Years of Age: Individualize thyroid function monitoring based on risk factors such as prematurity. (5.8)

6 ADVERSE REACTIONS

Most common adverse reactions (incidence ≥0.5%) are feeling hot, headache, nausea, chest pain, back pain, and vomiting. (6.1)

To report SUSPECTED ADVERSE REACTIONS, contact Bracco Diagnostics Inc. at 1-800-257-5181 or FDA at 1-800-FDA-1088 or www.fda.gov/medwatch.

8 USE IN SPECIFIC POPULATIONS

Lactation: A lactating woman may pump and discard breast milk for 10 hours after IOMERVU administration. (8.2)

FULL PRESCRIBING INFORMATION

WARNING: RISKS ASSOCIATED WITH INTRATHECAL ADMINISTRATION

Intrathecal administration, even if inadvertent, may cause death, convulsions, cerebral hemorrhage, coma, paralysis, arachnoiditis, acute renal failure, cardiac arrest, seizures, rhabdomyolysis, hyperthermia, and brain edema. IOMERVU is for intra-arterial or intravenous use only [see Dosage and Administration (2.1) and Warnings and Precautions (5.1)].

1 INDICATIONS AND USAGE

1.1 Intra-arterial Procedures†

IOMERVU is indicated for:

- Cerebral arteriography, including intra-arterial digital subtraction angiography (IA-DSA), in adults and pediatric patients
- Visceral and peripheral arteriography and aortography, including IA-DSA, in adults and pediatric patients
- Coronary arteriography and cardiac ventriculography in adults
- Radiographic evaluation of cardiac chambers and related arteries in pediatric patients

1.2 Intravenous Procedures†

IOMERVU is indicated for:

- Computed tomography (CT) of the head and body in adults and pediatric patients
- CT angiography of intracranial, visceral, and lower extremity arteries in adults and pediatric patients
- Coronary CT angiography in adults and pediatric patients
- CT urography in adults and pediatric patients

†Specific concentrations of IOMERVU are recommended for each type of imaging procedure [see Dosage and Administration (2.2, 2.3, 2.4, 2.5)].

2 DOSAGE AND ADMINISTRATION

2.1 Important Dosing and Administration Information

- IOMERVU is for intra-arterial or intravenous use only and must not be administered intrathecally [see Warnings and Precautions (5.1)].
- Specific concentrations of IOMERVU are recommended for each type of imaging procedure [see Dosage and Administration (2.2, 2.3, 2.4, 2.5)].
- Individualize the volume, concentration, and injection rate of IOMERVU within the specified ranges [see Dosage and Administration (2.2, 2.3, 2.4, 2.5)]. Consider factors such as age, body weight, vessel size, rate of blood flow within the vessel, anticipated pathology, degree and extent of opacification required, structures or area to be examined, disease processes affecting the patient, and equipment and technique to be employed.
- Hydrate patients before and after IOMERVU administration [see Warnings and Precautions (5.3)].
- Use aseptic technique for all handling and administration of IOMERVU.
- IOMERVU may be administered at either body temperature (37°C, 98.6°F) or room temperature (20°C to 25°C, 68°F to 77°F).
- Visually inspect IOMERVU for particulate matter or discoloration before administration, whenever the solution and container permit. Do not administer IOMERVU if particulate matter or discoloration is observed.
- Do not mix IOMERVU with, or inject in intravenous lines containing, other drugs or total nutritional admixtures.
- Each single-dose container of IOMERVU injection is intended for one procedure only. Discard any unused portion.

2.2 Recommended Dosage for Intra-arterial Procedures in Adults

- Recommended doses of IOMERVU in adults for intra-arterial procedures are shown in Table 1.
- Inject at rates approximately equal to the flow rate in the vessel being injected.

Table 1. Recommended Concentrations and Volumes of IOMERVU to Administer per Single Injection into Selected Arteries for Intra-arterial Procedures in Adults
Imaging Procedure | Concentration (mg Iodine/mL) | Volume (mL) | Maximum Total Dose (mL)
Cerebral arteriography | 300 | - Carotid, subclavian, and vertebral arteries: 6 mL to 12 mL - Aortic arch: 30 mL to 50 mL | 200 mL
Visceral and peripheral arteriography; aortography | 300 | - Aortography: 30 mL to 70 mL - Renal arteries: 10 mL to 12 mL - Other major branches of aorta: 20 mL to 60 mL | 200 mL
Intra-arterial digital subtraction angiography | 300 | - Carotid, subclavian, and vertebral arteries: 4 mL to 12 mL - Aortic arch: 20 mL to 25 mL - Aortography: 15 mL to 40 mL - Renal arteries: 6 mL to 16 mL - Other major branches of aorta: 10 mL to 40 mL - Ilio-femoral runoff: 8 mL to 40 mL | 200 mL
Coronary arteriography and cardiac ventriculography | 300 | - Coronary arteries: 3 mL to 7 mL - Cardiac ventriculography: 30 mL to 45 mL | 286 mL
Coronary arteriography and cardiac ventriculography | 350 | - Coronary arteries: 3 mL to 7 mL - Cardiac ventriculography: 30 mL to 45 mL | 245 mL
Coronary arteriography and cardiac ventriculography | 400 | - Coronary arteries: 3 mL to 7 mL - Cardiac ventriculography: 30 mL to 45 mL | 215 mL

2.3 Recommended Dosage for Intra-arterial Procedures in Pediatric Patients

- Recommended doses of IOMERVU in pediatric patients for intra-arterial procedures are shown in Table 2.
- Inject at rates approximately equal to the flow rate in the vessel being injected.

Table 2. Recommended Concentrations and Volumes per Body Weight of IOMERVU to Administer per Single Injection for Intra-arterial Procedures in Pediatric Patients
Imaging Procedure | Concentration (mg Iodine/mL) | Volume (mL/kg body weight) | Maximum Total Dose (mL/kg)
Cerebral arteriography | 300 | 0.5 mL/kg to 2 mL/kg | - 5 mL/kg - Do not exceed adult maximum dose (see Table 1)
Visceral and peripheral arteriography; aortography | 300 | 0.5 mL/kg to 2 mL/kg | - 5 mL/kg - Do not exceed adult maximum dose (see Table 1)
Intra-arterial digital subtraction angiography | 300 | 0.3 mL/kg to 1 mL/kg | - 5 mL/kg - Do not exceed adult maximum dose (see Table 1)
Radiographic evaluation of cardiac chambers and related arteries | 300, 350, or 400 | 0.5 mL/kg to 2 mL/kg | - 5 mL/kg - Do not exceed adult maximum dose (see Table 1)

2.4 Recommended Dosage for Intravenous Procedures in Adults

Recommended doses of IOMERVU in adults for intravenous procedures are shown in Table 3.

Table 3. Recommended Concentrations, Volumes, and Injection Rates of IOMERVU for Intravenous Procedures in Adults
Imaging Procedure | Concentration (mg Iodine/mL) | Volume (mL) | Injection Rate^3 (mL/s)
CT of Head and Body | 250 or 300 | 100 mL to 190 mL | 2 mL/s to 4 mL/s
CT of Head and Body | 350 or 400 | 75 mL to 150 mL | 2 mL/s to 4 mL/s
CT Angiography^1 | 300, 350, or 400 | 80 mL to 130 mL | 4 mL/s to 6 mL/s
Coronary CT Angiography^1 | 400 | 50 mL to 90 mL | 4 mL/s to 6 mL/s
CT Urography^2 | 350 | 90 mL to 120 mL | 2.5 mL/s

^1 The IOMERVU volume may be immediately followed by a 40 mL to 50 mL 0.9% sodium chloride injection flush at the same flow rate as the contrast volume.
^2 The IOMERVU volume may be administered either as a single bolus, or for dual-phase protocols as divided doses.
^3 The injection rate of IOMERVU should be determined according to the clinical indication and the location, size, and type of the intravenous access.

2.5 Recommended Dosage for Intravenous Procedures in Pediatric Patients

Recommended doses of IOMERVU in pediatric patients for intravenous procedures are shown in Table 4.

Table 4. Recommended Concentrations, Volumes per Body Weight, and Injection Rates of IOMERVU for Intravenous Procedures in Pediatric Patients
Imaging Procedure | Concentration (mg Iodine/mL) | Volume (mL/kg body weight) | Injection Rate (mL/s)*
CT of Head and Body | 250 or 300 | 1.5 mL/kg to 2.5 mL/kg | 1 mL/s to 2 mL/s
CT of Head and Body | 350 or 400 | 1 mL/kg to 2 mL/kg | 1 mL/s to 2 mL/s
CT Angiography | 300, 350, or 400 | 1 mL/kg to 2 mL/kg | 2 mL/s to 3 mL/s
Coronary CT Angiography | 300 or 400 | 1 mL/kg to 2 mL/kg | 2 mL/s to 3 mL/s
CT Urography | 300 | 1 mL/kg to 2 mL/kg | 1 mL/s to 2 mL/s

* The injection rate of IOMERVU should be determined according to the clinical indication and the location, size, and type of the intravenous access. In neonates and patients <15 kg in whom a 24-gauge angiocatheter is the only option, an injection rate of 1 mL/s is recommended.

3 DOSAGE FORMS AND STRENGTHS

Injection: clear, colorless to pale yellow solution available in the following iodine concentrations and configurations:

Concentration (mg Iodine/mL) | Package Size | Package Type
250 | 100 mL | Single-dose bottles
300 | 50 mL | Single-dose vials
300 | 100 mL, 150 mL, and 200 mL | Single-dose bottles
350 | 50 mL | Single-dose vials
350 | 100 mL, 150 mL, and 200 mL | Single-dose bottles
400 | 50 mL | Single-dose vials
400 | 100 mL, 150 mL, and 200 mL | Single-dose bottles

4 CONTRAINDICATIONS

None.

5 WARNINGS AND PRECAUTIONS

5.1 Risks Associated with Inadvertent Intrathecal Administration

IOMERVU is for intra-arterial or intravenous use only and must not be administered intrathecally [see Dosage and Administration (2.1)]. Intrathecal administration, even if inadvertent, can cause death, convulsions, cerebral hemorrhage, coma, paralysis, arachnoiditis, acute renal failure, cardiac arrest, seizures, rhabdomyolysis, hyperthermia, and brain edema.

5.2 Hypersensitivity Reactions

IOMERVU can cause life-threatening or fatal hypersensitivity reactions including anaphylaxis. Manifestations include respiratory arrest, laryngospasm, bronchospasm, angioedema, and shock [see Adverse Reactions (6.2)]. Most severe reactions develop shortly after the start of injection (e.g., within 1 to 3 minutes), but delayed reactions can occur. There is an increased risk in patients with a history of a previous reaction to contrast agents, and known allergic disorders (i.e., bronchial asthma, drug, or food allergies) or other hypersensitivities. Premedication with antihistamines or corticosteroids to minimize possible allergic reactions does not prevent serious life-threatening reactions, but may reduce their incidence and severity.

Obtain a history of allergy, hypersensitivity, and hypersensitivity reactions to iodinated contrast agents. Always have emergency resuscitation equipment and trained personnel available before use of IOMERVU. Monitor all patients for hypersensitivity reactions.

5.3 Acute Kidney Injury

Acute kidney injury, including renal failure, may occur after IOMERVU administration. Risk factors include pre-existing renal impairment, dehydration, diabetes mellitus, heart failure, advanced vascular disease, advanced age, concomitant use of nephrotoxic or diuretic medications, multiple myeloma or other paraproteinemia, and repetitive or large doses of IOMERVU.

Use the lowest necessary dose of IOMERVU in patients with renal impairment. Adequately hydrate patients prior to and following IOMERVU administration. Do not use laxatives, diuretics, or preparatory dehydration prior to IOMERVU administration.

5.4 Cardiovascular Adverse Reactions

IOMERVU increases the circulatory osmotic load and may induce acute or delayed hemodynamic disturbances in patients with heart failure, severely impaired renal function, combined renal and hepatic disease, or combined renal and cardiac disease, particularly when repetitive or large doses are administered.

Life-threatening or fatal cardiovascular reactions including hypotension, shock, and cardiac arrest have occurred with the use of IOMERVU. Most deaths occur within 10 minutes of injection, with cardiovascular disease as the main underlying factor. Cardiac decompensation, serious arrhythmias, and myocardial ischemia or infarction can occur during coronary arteriography and ventriculography.

Based upon literature reports, deaths from the administration of iodinated contrast agents range from 6.6 per 1 million (0.00066 percent) to 1 in 10,000 patients (0.01 percent). Use the lowest necessary dose of IOMERVU in patients with heart failure and always have emergency resuscitation equipment and trained personnel available. Monitor all patients for severe cardiovascular reactions.

5.5 Thromboembolic Events

Serious, in some cases fatal, thromboembolic events including myocardial infarction and stroke can occur during angiographic procedures with iodinated contrast agents including IOMERVU. During these procedures, increased thrombosis and activation of the complement system can occur. Risk factors for developing thromboembolic events include length of procedure, catheter and syringe material, underlying disease state, and concomitant medications.

To reduce risk of thromboembolic events, use meticulous angiographic techniques and minimize the length of the procedure. Avoid blood remaining in contact with syringes containing IOMERVU, which increases the risk of clotting. Avoid angiocardiography in patients with homocystinuria because of the risk of inducing thrombosis and embolism.

5.6 Extravasation and Injection Site Reactions

Extravasation can occur with IOMERVU administration, particularly in patients with severe arterial or venous disease. Inflammation, blistering, skin necrosis, and compartment syndrome have been reported following extravasation. In addition, injection site reactions such as pain and swelling at the injection site can also occur [see Adverse Reactions (6.1, 6.2)]. Ensure intravascular placement of catheters prior to injection. Monitor patients for extravasation and advise patients to seek medical care for progression of symptoms.

5.7 Thyroid Storm in Patients with Hyperthyroidism

Thyroid storm has occurred after the intravascular use of iodinated contrast agents in patients with hyperthyroidism or with an autonomously functioning thyroid nodule. Evaluate the risk in such patients before use of IOMERVU.

5.8 Thyroid Dysfunction in Pediatric Patients 0 Years to 3 Years of Age

Thyroid dysfunction characterized by hypothyroidism or transient thyroid suppression has been reported after both single exposure and multiple exposures to iodinated contrast agents in pediatric patients 0 years to 3 years of age.

Younger age, very low birth weight, prematurity, underlying medical conditions affecting thyroid function, admission to neonatal or pediatric intensive care units, and congenital cardiac conditions are associated with an increased risk of hypothyroidism after iodinated contrast agent exposure. Pediatric patients with congenital cardiac conditions may be at greatest risk given that they often require high doses of contrast during invasive cardiac procedures.

An underactive thyroid during early life may be harmful for cognitive and neurological development and may require thyroid hormone replacement therapy. After exposure to IOMERVU, individualize thyroid function monitoring based on underlying risk factors, especially in term and preterm neonates.

5.9 Hypertensive Crisis in Patients with Pheochromocytoma

Hypertensive crisis has occurred after the use of iodinated contrast agents in patients with pheochromocytoma. Closely monitor patients when administering IOMERVU if pheochromocytoma or catecholamine-secreting paragangliomas are suspected. Inject the minimum amount of IOMERVU necessary, assess blood pressure throughout the procedure, and have measures for treatment of a hypertensive crisis readily available.

5.10 Sickle Cell Crisis in Patients with Sickle Cell Disease

Iodinated contrast agents when administered intravascularly may promote sickling in individuals who are homozygous for sickle cell disease. Hydrate patients prior to and following IOMERVU administration and use IOMERVU only if the necessary imaging information cannot be obtained with alternative imaging modalities.

5.11 Severe Cutaneous Adverse Reactions

Severe cutaneous adverse reactions (SCAR) may develop from 1 hour to several weeks after intravascular contrast agent administration. These reactions include Stevens-Johnson syndrome and toxic epidermal necrolysis (SJS/TEN), acute generalized exanthematous pustulosis (AGEP), and drug reaction with eosinophilia and systemic symptoms (DRESS). Reaction severity may increase and time to onset may decrease with repeat administration of a contrast agent; prophylactic medications may not prevent or mitigate severe cutaneous adverse reactions. Avoid administering IOMERVU to patients with a history of a severe cutaneous adverse reaction to IOMERVU.

5.12 Interference with Laboratory Tests

IOMERVU can interfere with protein-bound iodine tests [see Drug Interactions (7.2)].

6 ADVERSE REACTIONS

The following clinically significant adverse reactions are described elsewhere in the labeling:

- Risks Associated with Intrathecal Administration [see Warnings and Precautions (5.1)]
- Hypersensitivity Reactions [see Warnings and Precautions (5.2)]
- Acute Kidney Injury [see Warnings and Precautions (5.3)]
- Cardiovascular Adverse Reactions [see Warnings and Precautions (5.4)]
- Thromboembolic Events [see Warnings and Precautions (5.5)]
- Extravasation and Injection Site Reactions [see Warnings and Precautions (5.6)]
- Thyroid Dysfunction in Pediatric Patients 0 Years to 3 Years of Age [see Warnings and Precautions (5.8)]
- Severe Cutaneous Adverse Reactions [see Warnings and Precautions (5.11)]

6.1 Clinical Trials Experience

Because clinical trials are conducted under widely varying conditions, adverse reaction rates observed in the clinical trials of a drug cannot be directly compared to rates in the clinical trials of another drug and may not reflect the rates observed in practice.

Adverse Reactions in Adult Patients

The safety of IOMERVU was evaluated in 4,621 adult patients who received 1,500 mg to 86,000 mg iodine doses of IOMERVU intra-arterially or intravenously in clinical trials. The average age was 60 years (range 18 years to 99 years), and 34% were female. The racial and ethnic distribution was 83% White, 10% Asian, 1% Black, 1% Hispanic, and 5% patients of other or unspecified groups.

Table 5 provides a summary of the adverse reactions reported in ≥0.5% of adult patients.

Table 5: Adverse Reactions Reported in ≥0.5% of 4,621 Adult Patients Receiving Intra-arterial or Intravenous Administration of IOMERVU in Clinical Trials
Adverse Reaction | Incidence (%)
Feeling hot | 2
Headache | 1.2
Nausea | 1
Chest pain | 0.6
Back pain | 0.5
Vomiting | 0.5

The following adverse reactions were observed in <0.5% of the adult patients receiving IOMERVU:

Blood and lymphatic system disorders: activated partial thromboplastin time prolonged, prothrombin time prolonged

Cardiovascular disorders: ventricular fibrillation, hypertensive crisis, coronary arteriospasm, congestive cardiac failure, cardiac flutter, atrioventricular block, right bundle branch block, hypotension, arrhythmia, bradycardia, supraventricular extrasystoles, ventricular extrasystoles, increased blood pressure, flushing

Ear and labyrinth disorders: vertigo, ear discomfort

Eye disorder: vision blurred, periorbital edema, photopsia

Gastrointestinal: esophageal varices hemorrhage, abdominal pain, abdominal distension, alanine aminotransferase (ALT) increased, constipation, diarrhea, dry mouth, salivary hypersecretion, oral paresthesia

General disorders: pain, injection site reactions (pain, discomfort, or warmth), peripheral edema, chills, asthenia, malaise

Musculoskeletal and connective tissue disorders: arthralgia, pain in jaw

Nervous system disorders: cerebrovascular disorder, dysarthria, visual field defect, burning sensation, presyncope, dizziness, dysgeusia, paresthesia

Psychiatric disorders: delirium, anxiety, insomnia

Renal and urinary disorders: acute kidney injury, increased blood creatinine, urinary urgency

Respiratory, thoracic, and mediastinal disorders: respiratory arrest, pulmonary edema, bronchospasm, dyspnea, cough, rhinitis, throat irritation or tightness, sneezing

Skin and subcutaneous tissue disorders: urticaria, blister, purpura, ecchymosis, rash, pruritus, erythema

Adverse Reactions in Pediatric Patients

The safety of IOMERVU was evaluated in 184 pediatric patients who received 1,800 mg to 76,000 mg iodine doses of IOMERVU intra-arterially or intravenously in clinical trials. The average age was 6 years (range 11 days to 17 years), and 47% were female. The racial distribution was 98% White, 1% Black, and 1% patients of other or unspecified groups. The overall character, quality, and severity of adverse reactions reported in pediatric patients were similar to those reported in adult patients.

6.2 Post Marketing Experience

The following adverse reactions have been identified during post-approval use of IOMERVU outside the United States. Because these reactions are reported voluntarily from a population of uncertain size, it is not always possible to reliably estimate their frequency or establish a causal relationship to drug exposure.

Blood and lymphatic system disorders: thrombocytopenia, leukopenia, leukocytosis

Cardiovascular disorders: cardio-respiratory arrest, circulatory collapse or shock, myocardial infarction, atrial fibrillation, cyanosis, pallor

Endocrine disorders: hyperthyroidism, hypothyroidism

Eye disorders: transient blindness, conjunctivitis, increased lacrimation

Gastrointestinal disorders: salivary gland enlargement, increased aspartate aminotransferase (AST), dysphagia

General disorders and administration site conditions:injection site swelling (usually due to extravasation)

Immune system disorders: hypersensitivity reactions including fatal anaphylaxis

Nervous system disorders: coma, loss of consciousness, encephalopathy, transient ischemic attack, paralysis, convulsion, syncope, amnesia, somnolence

Psychiatric disorders: confusional state

Respiratory, thoracic, and mediastinal disorders: acute respiratory distress syndrome (ARDS), laryngeal edema, pharyngeal edema, dysphonia

Skin and subcutaneous tissue disorders: severe reactions (Stevens-Johnson syndrome and toxic epidermal necrolysis (SJS/TEN), acute generalized exanthematous pustulosis (AGEP), drug reaction with eosinophilia and systemic symptoms (DRESS)) and mild reactions (rash, erythema, pruritus, urticaria, and skin discoloration)

7 DRUG INTERACTIONS

7.1 Drug-Drug Interactions

Metformin

Stop metformin at the time of, or prior to, IOMERVU administration in patients with an eGFR between 30 and 60 mL/min/1.73 m^2; in patients with a history of hepatic impairment, alcoholism, or heart failure; or in patients who will be administered intra-arterial iodinated contrast agents. Re-evaluate eGFR 48 hours after the imaging procedure, and reinstitute metformin only after renal function is stable.

Metformin can cause lactic acidosis in patients with renal impairment. Iodinated contrast agents appear to increase the risk of metformin-induced lactic acidosis, possibly as a result of worsening renal function.

Radioactive Iodine

Avoid thyroid therapy or testing using radioactive iodine for up to 6 weeks post IOMERVU. Administration of IOMERVU may interfere with thyroid uptake of radioactive iodine (I-131 and I-123) and decrease therapeutic and diagnostic efficacy.

7.2 Drug-Laboratory Test Interactions

Protein-Bound Iodine Test

Do not perform a protein-bound iodine test for at least 16 days following administration of IOMERVU.

Iodinated contrast agents, including IOMERVU, will temporarily increase protein-bound iodine in blood. However, thyroid function tests that do not depend on iodine estimations, e.g., triiodothyronine (T3) resin uptake and total or free thyroxine (T4) assays, are not affected.

8 USE IN SPECIFIC POPULATIONS

8.1 Pregnancy

Risk Summary

Available data from literature and postmarketing reports on iomeprol use in pregnant women over decades have not identified a drug-associated risk of major birth defects, miscarriage, or other adverse maternal or fetal outcomes. In animal reproduction studies, no adverse developmental outcomes were observed with intravenous administration of iomeprol to pregnant rats and rabbits at doses up to 0.45-times the maximum recommended human dose of 86,000 mg iodine. Animal studies show that iomeprol crosses the placenta (see Data).

The background risk of major birth defects and miscarriage for the indicated population is unknown. All pregnancies have a background risk of birth defects, loss or other adverse outcomes. In the U.S. general population, the estimated background risk of major birth defects and miscarriage in clinically recognized pregnancies is 2% to 4% and 15% to 20%, respectively.

Data

Animal Data

Embryo-fetal developmental toxicity studies were performed with intravenous administration of iomeprol in rats at daily doses of 600 mg, 1,500 mg, or 4,000 mg iodine/kg (0.07-, 0.17- or 0.45-fold the human equivalent dose (HED, mg/m^2) using the maximum human dose of 86,000 mg iodine per administration) from gestation days (GD) 6 to 15 and in rabbits at daily doses of 300 mg, 800 mg, or 2,000 mg iodine/kg (0.07-, 0.18- or 0.45-fold the HED using the maximum human dose of 86,000 mg iodine per administration) from GD 6 to 18. Iomeprol did not result in fetal harm at the highest doses evaluated, 0.45-times the maximum recommended human dose of 86,000 mg iodine.

A biodistribution study with a single intravenous administration of 1,000 mg iodine/kg (0.11-fold the HED using the maximum human dose of 86,000 mg iodine per administration) of radiolabeled iomeprol to pregnant rats showed that iomeprol crosses the placenta. No accumulation of radioactivity in fetal tissues was observed.

8.2 Lactation

Risk Summary

There are no data on the presence of iomeprol in human milk, the effects on the breastfed infant, or the effects on milk production. Iomeprol is present in animal milk (see Data). When a drug is present in animal milk, it is likely that the drug will be present in human milk. Iodinated contrast agents are excreted unchanged in human milk in very low amounts, with poor absorption from the gastrointestinal tract of a breastfed infant. The developmental and health benefits of breastfeeding should be considered along with the mother’s clinical need for IOMERVU and any potential adverse effects on the breastfed infant from IOMERVU or from the underlying maternal condition.

Clinical Considerations

Interruption of breastfeeding after exposure to iodinated contrast agents is not necessary because the potential exposure of the breastfed infant to iodine is small. However, a lactating woman may consider interrupting breastfeeding and pumping and discarding breast milk for 10 hours (approximately 5 elimination half-lives) after IOMERVU administration to minimize any potential drug exposure to a breastfed infant.

Data

An animal study with a single intravenous administration of 500 mg iodine/kg (0.06-fold the HED using the maximum human dose of 86,000 mg iodine per administration) of radiolabeled iomeprol to lactating rats showed that iomeprol rapidly distributed into the milk.

8.4 Pediatric Use

Intra-arterial Use

The safety and effectiveness of IOMERVU have been established in pediatric patients for cerebral, visceral, and peripheral arteriography, aortography including intra-arterial digital subtraction angiography, and radiographic evaluation of cardiac chambers and related arteries.

Use of IOMERVU is supported by evidence from adequate and well-controlled studies of IOMERVU in adults, pharmacokinetic data in pediatric patients aged 3 years to 17 years, pharmacokinetic simulation in pediatric patients younger than 3 years of age, and safety data obtained in 44 pediatric patients including 29 who were < 2 years of age, 14 children (2 years to 11 years), and 1 adolescent (12 years to 17 years). In general, adverse reactions reported in pediatric patients were similar to those in adults [see Adverse Reactions (6.1), Clinical Pharmacology (12.3), and Clinical Studies (14.1)].

Intravenous Use

The safety and effectiveness of IOMERVU have been established in pediatric patients for CT of the head and body, CT angiography of intracranial, visceral, and lower extremity arteries, coronary CT angiography, and CT urography.

Use of IOMERVU is supported by evidence from adequate and well-controlled studies of IOMERVU in adults, pharmacokinetic data in pediatric patients aged 3 years to 17 years, pharmacokinetic simulation in pediatric patients younger than 3 years of age, and safety data obtained in 140 pediatric patients including 22 who were < 2 years of age, 92 children (2 years to 11 years), and 26 adolescents (12 years to 17 years). In general, adverse reactions reported in pediatric patients were similar to those in adults [see Adverse Reactions (6.1), Clinical Pharmacology (12.3), and Clinical Studies (14.2)].

Intra-arterial and Intravenous Use

Pediatric patients at higher risk of experiencing an adverse reaction during and after administration of any contrast agent may include those with asthma, sensitivity to medication and/or allergens, cyanotic and acyanotic heart disease, heart failure, or serum creatinine greater than 1.5 mg/dL, or those less than 12 months of age. Pediatric patients with immature renal function or dehydration may be at increased risk for adverse events due to slower elimination of iodinated contrast agents [See Clinical Pharmacology (12.3)].

Thyroid function tests indicative of thyroid dysfunction, characterized by hypothyroidism or transient thyroid suppression have been reported following iodinated contrast agent administration in pediatric patients, including term and preterm neonates. Some patients were treated for hypothyroidism. After exposure to iodinated contrast agents, individualize thyroid function monitoring in pediatric patients 0 years to 3 years of age based on underlying risk factors, especially in term and preterm neonates [See Warnings and Precautions (5.8) and Adverse Reactions (6.2)].

8.5 Geriatric Use

Of the total number of subjects in clinical studies of IOMERVU, 1,977 (43%) patients were 65 years and older, while 629 (14%) patients were 75 years and older. No overall differences in safety or effectiveness were observed between these patients and younger patients.

Iomeprol is excreted by the kidneys, and the risk of adverse reactions to IOMERVU is greater in patients with renal impairment. Because elderly patients are more likely to have renal impairment, care should be taken in dose selection, and it may be useful to monitor renal function [see Warnings and Precautions (5.3) and Use in Specific Populations (8.6)].

8.6 Renal Impairment

Preexisting renal impairment increases the risk for acute kidney injury. Renal impairment reduces the rate of elimination of iomeprol. Iomeprol can be removed by dialysis [see Warnings and Precautions (5.3) and Clinical Pharmacology (12.3)].

10 OVERDOSAGE

The adverse effects of overdosage are life-threatening and affect mainly the pulmonary and cardiovascular systems. Treatment of an overdosage is directed toward the support of all vital functions and prompt institution of symptomatic therapy. Iomeprol can be removed by dialysis [see Clinical Pharmacology (12.3)].

11 DESCRIPTION

IOMERVU (iomeprol) injection is a tri-iodinated, non-ionic radiographic contrast agent for intra-arterial or intravenous use. It is provided as a sterile, nonpyrogenic, clear, colorless to pale yellow solution.

The chemical name for iomeprol is N,N’-bis(2,3-dihydroxypropyl)-5-[(hydroxyacetyl)-methylamino]-2,4,6-tri-iodo-1,3-benzenedicarboxamide. Iomeprol has a molecular formula of C17H22I3N3O8, a molecular weight of 777.09 (iodine content of 49%), and the following structural formula:

IOMERVU injection is available in four iodine concentrations:

- IOMERVU 250 mg Iodine/mL: Each mL contains 510 mg iomeprol (providing 250 mg bound iodine) and 1 mg tromethamine.
- IOMERVU 300 mg Iodine/mL: Each mL contains 612 mg iomeprol (providing 300 mg bound iodine) and 1 mg tromethamine.
- IOMERVU 350 mg Iodine/mL: Each mL contains 714 mg iomeprol (providing 350 mg bound iodine) and 1 mg tromethamine.
- IOMERVU 400 mg Iodine/mL: Each mL contains 816 mg iomeprol (providing 400 mg bound iodine) and 1 mg tromethamine.

The pH of IOMERVU has been adjusted to 6.5 to 7.2 with hydrochloric acid.

Physical characteristics are noted in Table 6. IOMERVU has osmolalities approximately 1.5 to 2.5 times that of plasma (285 mOsm/kg water) as shown in the table below and are hypertonic under conditions of use.

Table 6. Physical Characteristics of IOMERVU
Concentration (mg Iodine/mL) | Density (d^204 ± 0.0002) | Osmolality (mOsmol/kg) | Viscosity (mPa·s)
Concentration (mg Iodine/mL) | Density (d^204 ± 0.0002) | 37°C | 20°C | 37°C
250 | 1.278 | 435 | 4.9 | 2.9
300 | 1.334 | 521 | 8.1 | 4.5
350 | 1.390 | 618 | 14.5 | 7.5
400 | 1.446 | 726 | 27.5 | 12.6

12 CLINICAL PHARMACOLOGY

12.1 Mechanism of Action

Iomeprol is a radiographic iodinated contrast agent that opacifies the vessels and body structures where the contrast agent is present following intravenous or intra-arterial administration, permitting radiographic visualization of the internal structures through attenuation of X-ray photons.

In imaging of the body, iodinated contrast agents diffuse from the vessels into the extravascular space. In normal brain with an intact blood-brain barrier, the contrast agent does not diffuse into the extravascular space and contrast enhancement is generally due to the presence of contrast within the vascular space. In patients with a disrupted blood-brain barrier, the contrast agent accumulates in the extravascular space in the region of disruption.

12.2 Pharmacodynamics

The degree of radiographic enhancement by iomeprol is related to the iodine concentration in the tissue of interest following the administration of IOMERVU. However, the exposure-response relationships and time course of pharmacodynamic response of iomeprol have not been fully characterized.

12.3 Pharmacokinetics

The pharmacokinetic parameters of iomeprol are presented as mean (standard deviation, SD) unless otherwise specified.

The maximum concentration (Cmax) and area under the concentration-time curve (AUC) are dose-proportional across the dose range of 250 mg iodine/kg to 1,250 mg iodine/kg body weight.

Distribution
The volume of distribution of iomeprol is 0.28 (0.05) L/kg. Iomeprol does not bind to plasma proteins.

Elimination
The elimination half-life of iomeprol is 1.8 (0.33) hours and the total body clearance is 0.10 (0.01) L/hr/kg.

Metabolism
Iomeprol does not undergo significant metabolism.

Excretion
Approximately 90% of the iomeprol dose is excreted unchanged in urine within 24 hours.

Specific Populations

Pediatric Patients

No clinically significant differences in the pharmacokinetics of iomeprol were observed in pediatric patients aged 3 years to 17 years compared to adult patients who received IOMERVU. No clinically significant differences in Cmax and concentration of iomeprol within 5 minutes after IOMERVU administration between pediatric patients younger than 3 years of age and adults are expected based on pharmacokinetic simulations.

Patients with Renal Impairment
The renal clearance of iomeprol decreased by 28% in patients with mild (GFR 51 − 75 mL/min, estimated by inulin clearance (CLinulin)), 66% with moderate (GFR 26 − 50 mL/min, by CLinulin), and 84% with severe (GFR ≤ 25 mL/min, by CLinulin) renal impairment. Similarly, mean half-life increased 1.6-fold in mild, 2.9-fold in moderate, and 6.4-fold in severe renal impairment.

Iomeprol is dialyzable. Iomeprol plasma concentrations decreased by 83% in patients with severe renal impairment who underwent hemodialysis 2 hours after a single administration of a 20,000 mg iodine dose of IOMERVU by intravenous route.

13 NONCLINICAL TOXICOLOGY

13.1 Carcinogenesis, Mutagenesis, Impairment of Fertility

Carcinogenesis
No carcinogenicity studies of iomeprol have been conducted.

Mutagenesis
Iomeprol did not demonstrate mutagenic or clastogenic potential in an in vitro bacterial reverse mutation assay (Ames test) or in an in vivo rat bone marrow micronucleus assay.

Impairment of Fertility

Iomeprol did not impair the fertility of male or female rats when intravenously administered at doses up to 0.45-times the maximum recommended human dose.

14 CLINICAL STUDIES

14.1 Intra-arterial Studies

Cerebral arteriography was evaluated in one blinded read study incorporating two prospective, randomized, double-blind, multi-center clinical studies of 61 adult patients (35 male, 26 female) who were administered IOMERVU 300 mg Iodine/mL by intra-arterial route. The mean age was 52 years (range 17 years to 86 years), and 23% of patients were ≥65 years old. The mean total iodine dose administered was 29,000 mg. The racial and ethnic representations were 62% White, 15% Black, 20% Hispanic, and 3% Asian. Visualization was independently assessed as adequate or inadequate by three blinded readers. Visualization was rated as adequate in 100% of patients.

Visceral and peripheral arteriography were evaluated in one blinded read study incorporating two prospective, randomized, double-blind, multi-center clinical studies of 60 adult patients (36 male, 24 female) who were administered IOMERVU 300 mg Iodine/mL by intra-arterial route. The mean age was 67 years (range 29 years to 95 years) and 62% of patients were ≥65 years old. The mean total iodine dose administered was 48,000 mg. The racial and ethnic representations were 92% White, 7% Black, and 1% Hispanic. Visualization was independently assessed as adequate or inadequate by three blinded readers. Visualization was rated as adequate in 98% of patients.

Similar cerebral arteriography, visceral arteriography, and peripheral arteriography studies with digital subtraction angiography (DSA) were completed with comparable findings.

Coronary arteriography and cardiac ventriculography were evaluated in one blinded read study incorporating four prospective, randomized, double-blind, multi-center clinical studies of 59 adult patients (41 male, 18 female) who were administered IOMERVU 400 mg Iodine/mL, and 59 adult patients (43 male, 16 female) who were administered IOMERVU 300 mg Iodine/mL by intra-arterial route. The mean age was 60 years (range 22 years to 85 years), and 42% of patients were ≥65 years old. The mean total iodine dose administered was 45,000 mg. The racial and ethnic representations were 75% White, 15% Black, 6% Hispanic, 1% Asian, and 3% other racial or ethnic groups. Visualization was independently assessed as adequate or inadequate by three blinded readers. Visualization was rated as adequate in 93% - 100% of patients for both concentrations.

14.2 Intravenous Studies

CT of the head and body was evaluated in one blinded read study incorporating four prospective, randomized, double-blind, multi-center clinical studies of 59 adult patients (22 male, 37 female) who were administered IOMERVU 400 mg Iodine/mL and 59 adult patients (26 male, 33 female) who were administered IOMERVU 250 mg Iodine/mL by intravenous route. The mean age was 55 years (range 19 years to 80 years), and 30% of patients were ≥65 years old. The mean total iodine dose administered was 41,000 mg. The racial and ethnic representations were 78% White, 16% Black, 4% Hispanic, 1% Asian, and 1% other racial or ethnic groups. Visualization was independently assessed as adequate or inadequate by three blinded readers. Visualization was rated as adequate in 98% - 100% of patients for both concentrations.

CT angiography was evaluated in two prospective, single-center clinical studies enrolling a total of 262 adult patients (202 male, 60 female) with suspected or known peripheral arterial disease who were administered IOMERVU 400 mg Iodine/mL by intravenous route. The mean age was 62 years (range 36 years to 88 years). Both studies assessed the diagnostic performance for detection of significant stenosis at the arterial segment level using digital subtraction angiography as the reference standard. In the first study, 212 patients (7,392 segments, 42% positive by reference standard) were independently evaluated by three blinded readers. The reported segment-level sensitivity and specificity (95% confidence interval) for the detection of ≥70% stenosis were 99% (98%, 99%) and 97% (96%, 97%), respectively. In the second study, 50 patients (929 to 933 lesions, 34% positive by reference standard) were evaluated by two blinded readers. The reported lesion-level sensitivity and specificity (95% confidence interval) for the detection of >50% stenosis were 93% (91%, 96%) and 97% (95%, 98%), respectively, for reader 1 and 90% (87%, 93%) and 96% (94%, 97%), respectively, for reader 2.

Coronary CT angiography was evaluated in two prospective, single-center clinical studies enrolling a total of 301 adult patients (259 male, 42 female) with suspected coronary artery disease who were administered IOMERVU 400 mg Iodine/mL by intravenous route. The mean age was 64 years. Both studies assessed the diagnostic performance for detection of ≥50% stenosis at the coronary artery segment level using invasive coronary angiography as the reference standard. In the first study, 210 patients (2,532 segments, 22% positive by reference standard) were independently evaluated by two blinded readers with discrepancies resolved by consensus. The segment-level sensitivity and specificity (95% confidence interval) were 84% (81%, 87%) and 94% (92%, 95%), respectively. In the second study, 91 patients (1,456 segments, 18% positive by reference standard) were independently evaluated by two blinded readers with discrepancies resolved by a third reader. The segment-level sensitivity and specificity (95% confidence interval) were 97% (95%, 99%) and 91% (89%, 92%), respectively.

CT urography was evaluated in two retrospective, single-center clinical studies of 185 adult patients (130 male, 55 female) who were administered IOMERVU 350 mg Iodine/mL by intravenous route. The mean age was 55 years (range 20 years to 89 years). In the first study, two readers assessed parenchymal image quality on a 3-point scale (inadequate, diagnostic, or very good or excellent) as very good or excellent in 64% to 98% of the patients depending on scan protocol. In the second study, two blinded readers assessed visualization quality for the urinary system overall (calyces, renal pelvis, ureter, and bladder), on a scale of 0 (absence of visualization) to 5 (excellent visualization), with the mean score (SD) for reader 1 being 4.2 (1.4) and for reader 2 being 4.1 (1.5).

16 HOW SUPPLIED/STORAGE AND HANDLING

How Supplied

IOMERVU (iomeprol) injection is a clear, colorless to pale yellow solution supplied in clear glass single-dose vials or bottles in the following configurations:

Concentration (mg Iodine/mL) | Packages Size | Package Type | Sale Unit | NDC
250 | 100 mL | Single-dose bottles | Carton of 10 | 0270-7013-14
300 | 50 mL | Single-dose vials | Carton of 10 | 0270-7016-15
300 | 100 mL | Single-dose bottles | Carton of 10 | 0270-7016-17
300 | 150 mL | Single-dose bottles | Carton of 10 | 0270-7016-18
300 | 200 mL | Single-dose bottles | Carton of 10 | 0270-7016-19
350 | 50 mL | Single-dose vials | Carton of 10 | 0270-7017-20
350 | 100 mL | Single-dose bottles | Carton of 10 | 0270-7017-21
350 | 150 mL | Single-dose bottles | Carton of 10 | 0270-7017-24
350 | 200 mL | Single-dose bottles | Carton of 10 | 0270-7017-25
400 | 50 mL | Single-dose vials | Carton of 10 | 0270-7018-26
400 | 100 mL | Single-dose bottles | Carton of 10 | 0270-7018-27
400 | 150 mL | Single-dose bottles | Carton of 10 | 0270-7018-28
400 | 200 mL | Single-dose bottles | Carton of 10 | 0270-7018-29

Storage and Handling

Store at 20°C to 25°C (68°F to 77°F) [see USP Controlled Room Temperature]. Keep in original carton with the cover closed to protect from light. Do not freeze.

17 PATIENT COUNSELING INFORMATION

Hypersensitivity Reactions

Advise the patient concerning the risk of hypersensitivity reactions that can occur both during and after IOMERVU administration. Advise the patient to report any signs or symptoms of hypersensitivity reactions during the procedure and to seek immediate medical attention for any signs or symptoms experienced after discharge [see Warnings and Precautions (5.2)].

Advise patients to inform their physician if they develop a rash after receiving IOMERVU [see Warnings and Precautions (5.11)].

Acute Kidney Injury

Advise the patient concerning appropriate hydration to decrease the risk of kidney injury [see Warnings and Precautions (5.3)].

Extravasation

If extravasation occurs during injection, advise patients to seek medical care for progression of symptoms [see Warnings and Precautions (5.6)].

Thyroid Dysfunction

Advise parents or caregivers about the risk of developing thyroid dysfunction after IOMERVU administration. Advise parents or caregivers about when to seek medical care for their child to monitor for thyroid dysfunction [see Warnings and Precautions (5.8)].

Lactation

Advise a lactating woman that interruption of breastfeeding is not necessary, however, to avoid any exposure a lactating woman may consider pumping and discarding breast milk for 10 hours after IOMERVU administration [see Use in Specific Populations (8.2)].

Manufactured for
Bracco Diagnostic Inc.
Princeton, NJ 08540

Manufactured by
BIPSO GmbH
78224 Singen (Germany)

PACKAGE LABEL

Iomervu Labels